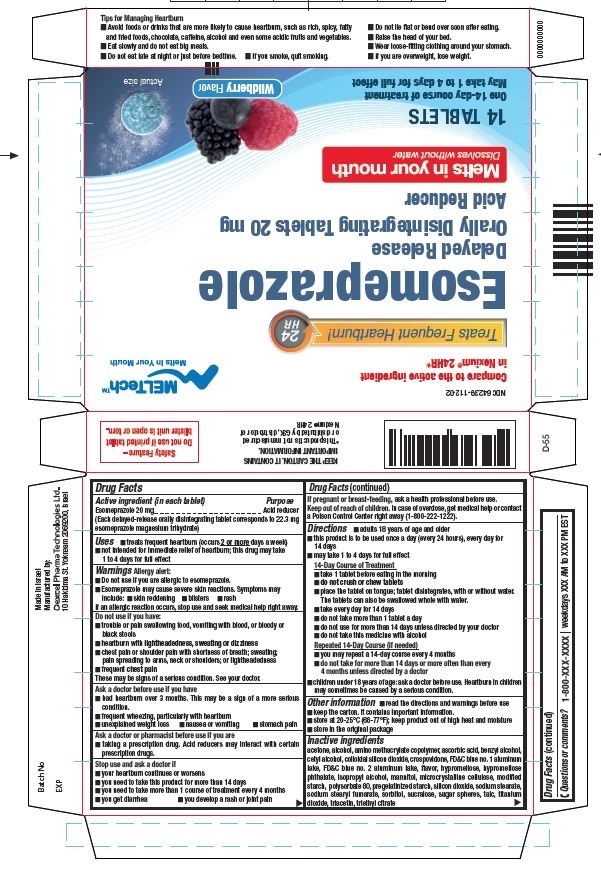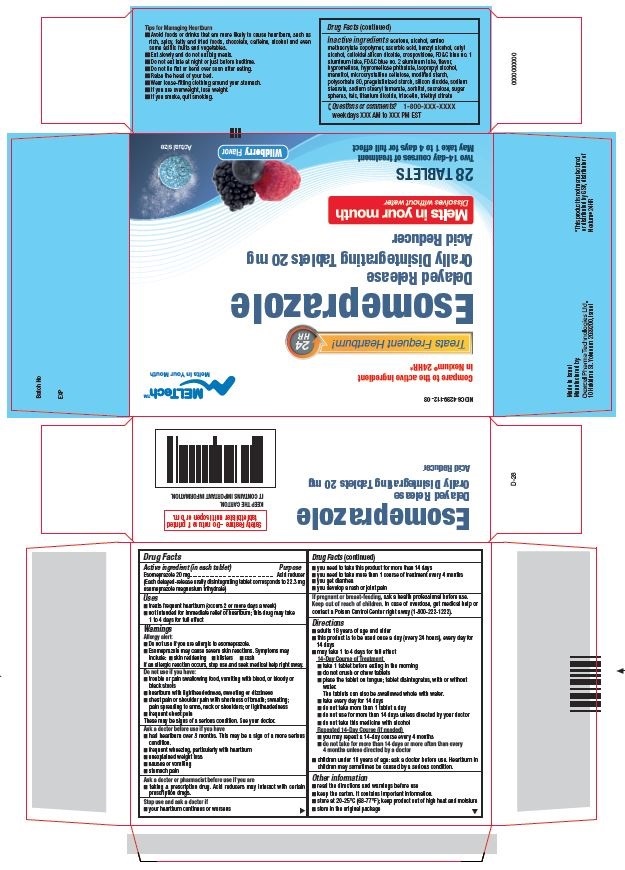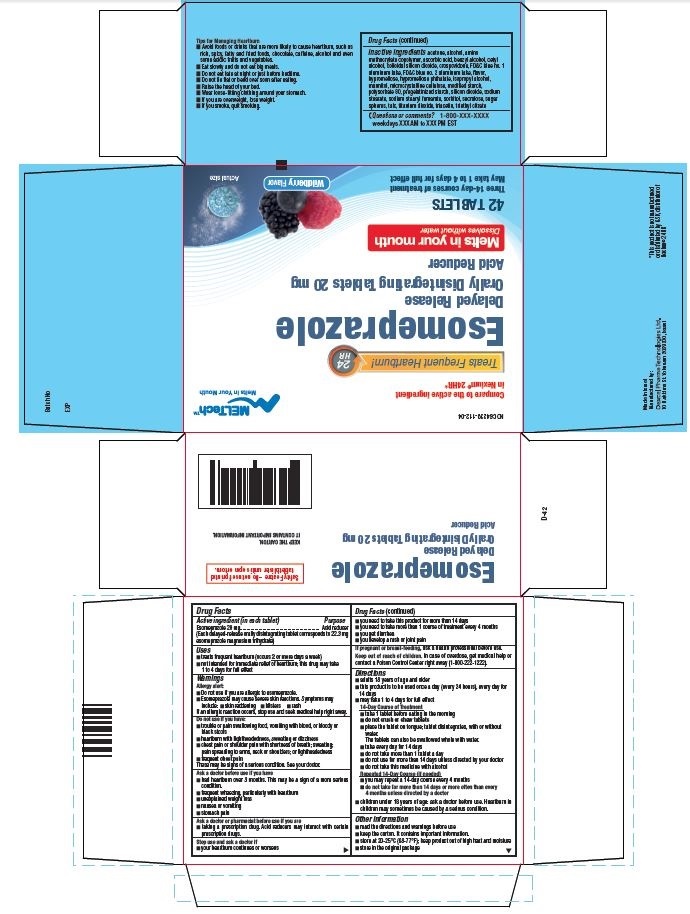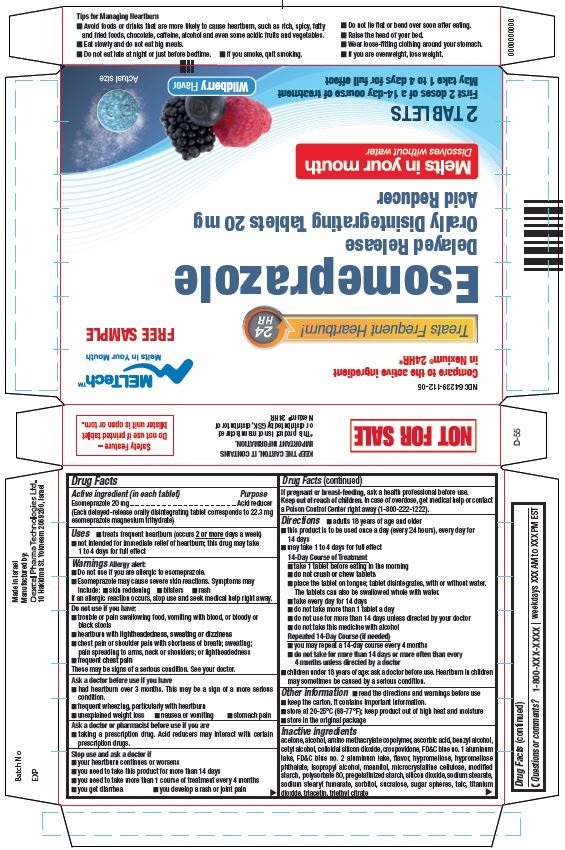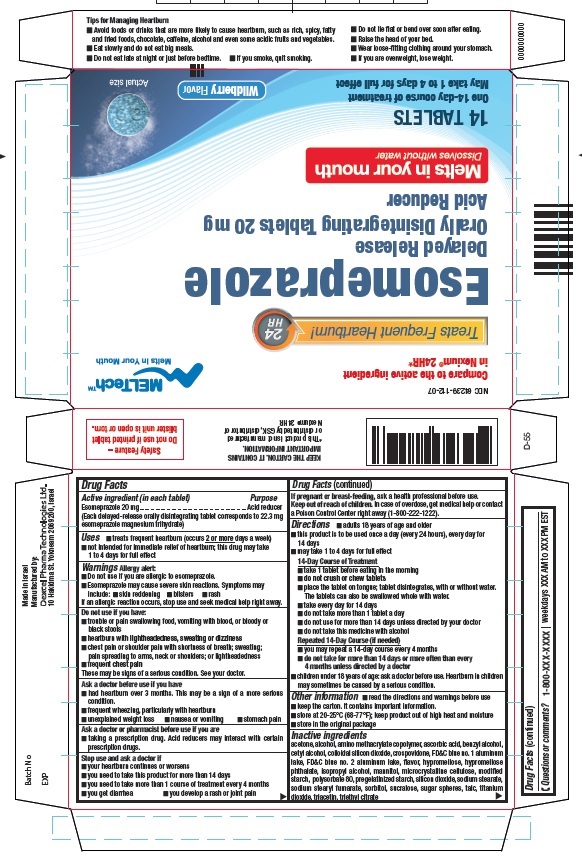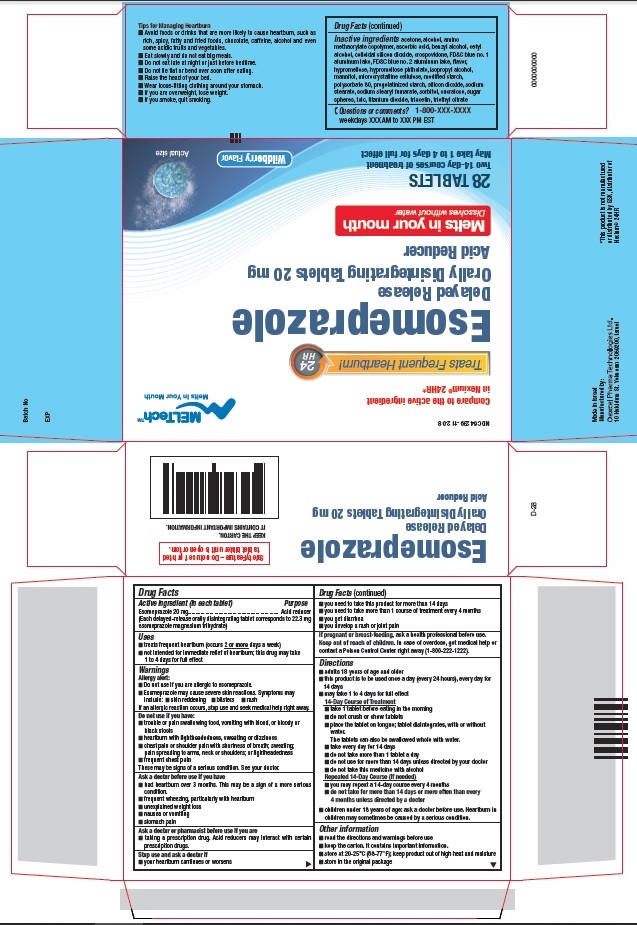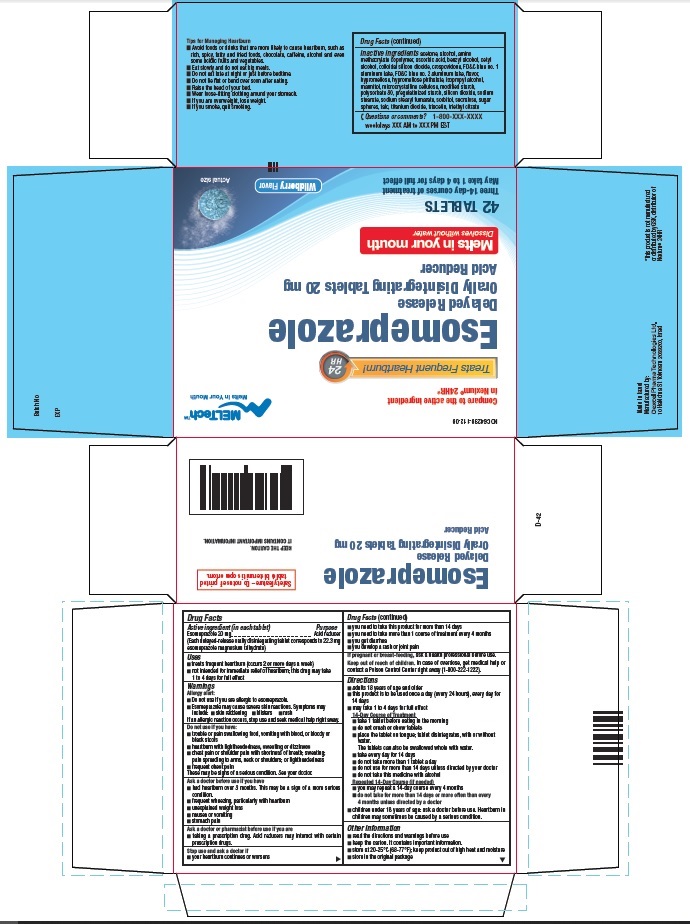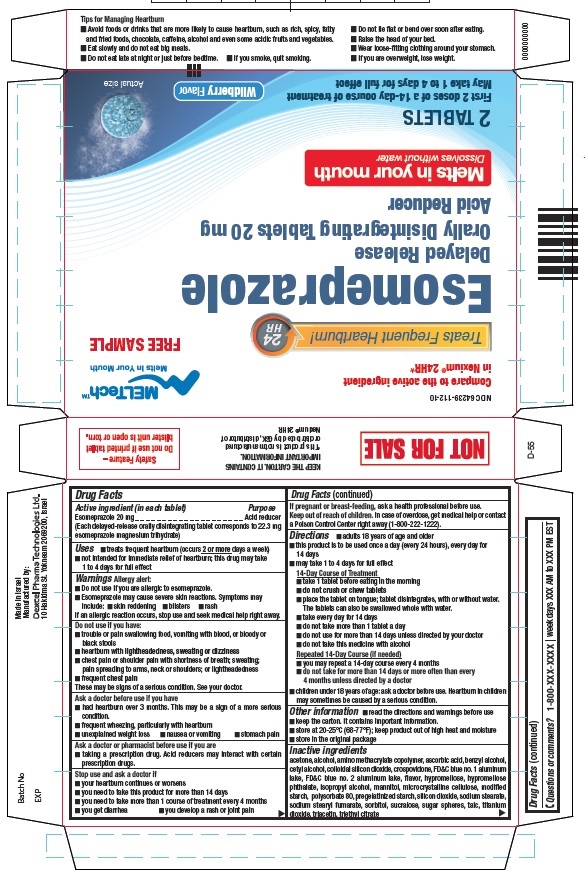 DRUG LABEL: Esomeprazole
NDC: 64239-112 | Form: TABLET, ORALLY DISINTEGRATING, DELAYED RELEASE
Manufacturer: Dexcel Pharma Technologies Ltd
Category: otc | Type: HUMAN OTC DRUG LABEL
Date: 20250109

ACTIVE INGREDIENTS: Esomeprazole 20 mg/1 1
INACTIVE INGREDIENTS: ACETONE; ALCOHOL; DIMETHYLAMINOETHYL METHACRYLATE - BUTYL METHACRYLATE - METHYL METHACRYLATE COPOLYMER; ASCORBIC ACID; BENZYL ALCOHOL; CETYL ALCOHOL; CROSPOVIDONE; FD&C BLUE NO. 1--ALUMINUM LAKE; FD&C BLUE NO. 2--ALUMINUM LAKE; HYPROMELLOSE 2910 (5 MPA.S); HYPROMELLOSE PHTHALATE (31% PHTHALATE, 170 CST); ISOPROPYL ALCOHOL; MANNITOL; MICROCRYSTALLINE CELLULOSE; MODIFIED CORN STARCH (1-OCTENYL SUCCINIC ANHYDRIDE); POLYSORBATE 80; SILICON DIOXIDE; SODIUM STEARATE; SODIUM STEARYL FUMARATE; SORBITOL; STARCH, CORN; SUCRALOSE; SUCROSE; TALC; TITANIUM DIOXIDE; TRIACETIN; TRIETHYL CITRATE

Esomeprazole Delayed Release Orally Disintegrating Tablets, 20 mg

Drug Facts

Active ingredient (in each tablet)

Esomeprazole 20 mg

(Each delayed-release tablet corresponds to 22.3 mg

esomeprazole magnesium trihydrate)

Purpose

Acid reducer

Uses

- treats frequent heartburn (occurs 2 or more days a week)
- not intended for immediate relief of heartburn; this drug may take 1 to 4 days for full effect

Warnings

Allergy alert: Do not use if you are allergic to esomeprazole

DO NOT USE

- Esomeprazole may cause severe skin reactions. Symptoms may include: ■ skin reddening ■ blisters ■ rash

If an allergic reaction occurs, stop use and seek medical help right away.

Do not use if you have:

- trouble or pain swallowing food, vomiting with blood, or bloody or black stools
- heartburn with lightheadedness, sweating or dizziness
- chest pain or shoulder pain with shortness of breath; sweating; pain spreading to arms, neck or shoulders; or lightheadedness
- frequent chest pain

These may be signs of a serious condition. See your doctor.

Ask a doctor before use if you have

- had heartburn over 3 months. This may be a sign of a more serious condition.
- frequent wheezing, particularly with heartburn
- unexplained weight loss
- nausea or vomiting
- stomach pain

Ask a doctor or pharmacist before use if you are

- taking a prescription drug. Acid reducers may interact with certain prescription drugs.

Stop use and ask a doctor if

- your heartburn continues or worsens
- you need to take this product for more than 14 days
- you need to take more than 1 course of treatment every 4 months
- you get diarrhea
- you develop a rash or joint pain

PREGNANCY OR BREAST FEEDING

If pregnant or breast-feeding, ask a health professional before use.

Keep out of reach of children. In case of overdose, get medical help or contact a Poison Control Center right away (1-800-222-1222).

Directions

- adults 18 years of age and older
- this product is to be used once a day (every 24 hours), every day for 14 days
- may take 1 to 4 days for full effect

DOSAGE AND ADMINISTRATION

14-Day Course of Treatment

- take 1 tablet before eating in the morning
- do not crush or chew tablets
- place the tablet on tongue; tablet disintegrates, with or without water. The tablets can also be swallowed whole with water.
- take every day for 14 days
- do not take more than 1 tablet a day
- do not use for more than 14 days unless directed by your doctor
- do not take this medicine with alcohol

PATIENT COUNSELING INFORMATION

Repeated 14-Day Courses (if needed)

- you may repeat a 14-day course every 4 months
- do not take for more than 14 days or more often than every 4 months unless directed by a doctor
- children under 18 years of age: ask a doctor before use. Heartburn in children may sometimes be caused by a serious condition.

Other information

- read the directions and warnings before use
- keep the carton. It contains important information
- store at 20-25°C (68-77°F); keep product out of high heat and moisture
- store in the original package

Inactive ingredients

acetone, alcohol, amino methacrylate copolymer, ascorbic acid, benzyl alcohol, cetyl alcohol, colloidal silicon dioxide, crospovidone, FD&C blue no. 1 aluminum lake, FD&C blue no. 2 aluminum lake, flavor, hypromellose, hypromellose phthalate, isopropyl alcohol, mannitol, microcrystalline cellulose, modified starch, polysorbate 80, pregelatinized starch, silicon dioxide, sodium stearate, sodium stearyl fumarate, sorbitol, sucralose, sugar spheres, talc, titanium dioxide, triacetin, triethyl citrate

Questions or comments? 1-800-XXX-XXXX:

Weekdays XXX AM to XXX PM EST

Tips for Managing Heartburn

- Avoid foods or drinks that are more likely to cause heartburn, such as rich, spicy, fatty and fried foods, chocolate, caffeine, alcohol and even some acidic fruits and vegetables.
- Eat slowly and do not eat big meals.
- Do not eat late at night or just before bedtime.
- Do not lie flat or bend over soon after eating.
- Raise the head of your bed.
- Wear loose-fitting clothing around your stomach.
- If you are overweight, lose weight.
- If you smoke, quit smoking.

PACKAGE LABEL

NDC 64239-112-02

MELTechTM

Melts in Your Mouth

Compare to the active ingredient in Nexium® 24HR*

Treats Frequent Heartburn! 24HR

Esomeprazole

Delayed Release

Orally Disintegrating Tablets 20 mg

Acid Reducer

Melts in your mouth

Dissolves without water

14 TABLETS

One 14-day course of treatment

May take 1 to 4 days for full effect

Wildberry Flavor

Actual size

PACKAGE LABEL

NDC 64239-112-03

MELTechTM

Melts in Your Mouth

Compare to the active ingredient in Nexium® 24HR*

Treats Frequent Heartburn! 24HR

Esomeprazole

Delayed Release

Orally Disintegrating Tablets 20 mg

Acid Reducer

Melts in your mouth

Dissolves without water

28 TABLETS

Two 14-day courses of treatment

May take 1 to 4 days for full effect

Wildberry Flavor

Actual size

PACKAGE LABEL

NDC 64239-112-04

MELTechTM

Melts in Your Mouth

Compare to the active ingredient in Nexium® 24HR*

Treats Frequent Heartburn! 24HR

Esomeprazole

Delayed Release

Orally Disintegrating Tablets 20 mg

Acid Reducer

Melts in your mouth

Dissolves without water

42 TABLETS

Three 14-day courses of treatment

May take 1 to 4 days for full effect

Wildberry Flavor

Actual size

PACKAGE LABEL

NDC 64239-112-05

MELTechTM

Melts in Your Mouth

FREE SAMPLE

Compare to the active ingredient in Nexium® 24HR*

Treats Frequent Heartburn! 24HR

Esomeprazole

Delayed Release

Orally Disintegrating Tablets 20 mg

Acid Reducer

Melts in your mouth

Dissolves without water

2 TABLETS

First 2 doses of a 14-day course of treatment

May take 1 to 4 days for full effect

Wildberry Flavor

Actual size

PACKAGE LABEL

NDC 64239-112-07

MELTechTM

Melts in Your Mouth

Compare to the active ingredient in Nexium® 24HR*

Treats Frequent Heartburn! 24HR

Esomeprazole

Delayed Release

Orally Disintegrating Tablets 20 mg

Acid Reducer

Melts in your mouth

Dissolves without water

14 TABLETS

One 14-day course of treatment

May take 1 to 4 days for full effect

Wildberry Flavor

Actual size

PACKAGE LABEL

NDC 64239-112-08

MELTechTM

Melts in Your Mouth

Compare to the active ingredient in Nexium® 24HR*

Treats Frequent Heartburn! 24HR

Esomeprazole

Delayed Release

Orally Disintegrating Tablets 20 mg

Acid Reducer

Melts in your mouth

Dissolves without water

28 TABLETS

Two 14-day courses of treatment

May take 1 to 4 days for full effect

Wildberry Flavor

Actual size

PACKAGE LABEL

NDC 64239-112-09

MELTechTM

Melts in Your Mouth

Compare to the active ingredient in Nexium® 24HR*

Treats Frequent Heartburn! 24HR

Esomeprazole

Delayed Release

Orally Disintegrating Tablets 20 mg

Acid Reducer

Melts in your mouth

Dissolves without water

42 TABLETS

Three 14-day courses of treatment

May take 1 to 4 days for full effect

Wildberry Flavor

Actual size

PACKAGE LABEL

NDC 64239-112-10

MELTechTM

Melts in Your Mouth

FREE SAMPLE

Compare to the active ingredient in Nexium® 24HR*

Treats Frequent Heartburn! 24HR

Esomeprazole

Delayed Release

Orally Disintegrating Tablets 20 mg

Acid Reducer

Melts in your mouth

Dissolves without water

2 TABLETS

First 2 doses of a 14-day course of treatment

May take 1 to 4 days for full effect

Wildberry Flavor

Actual size